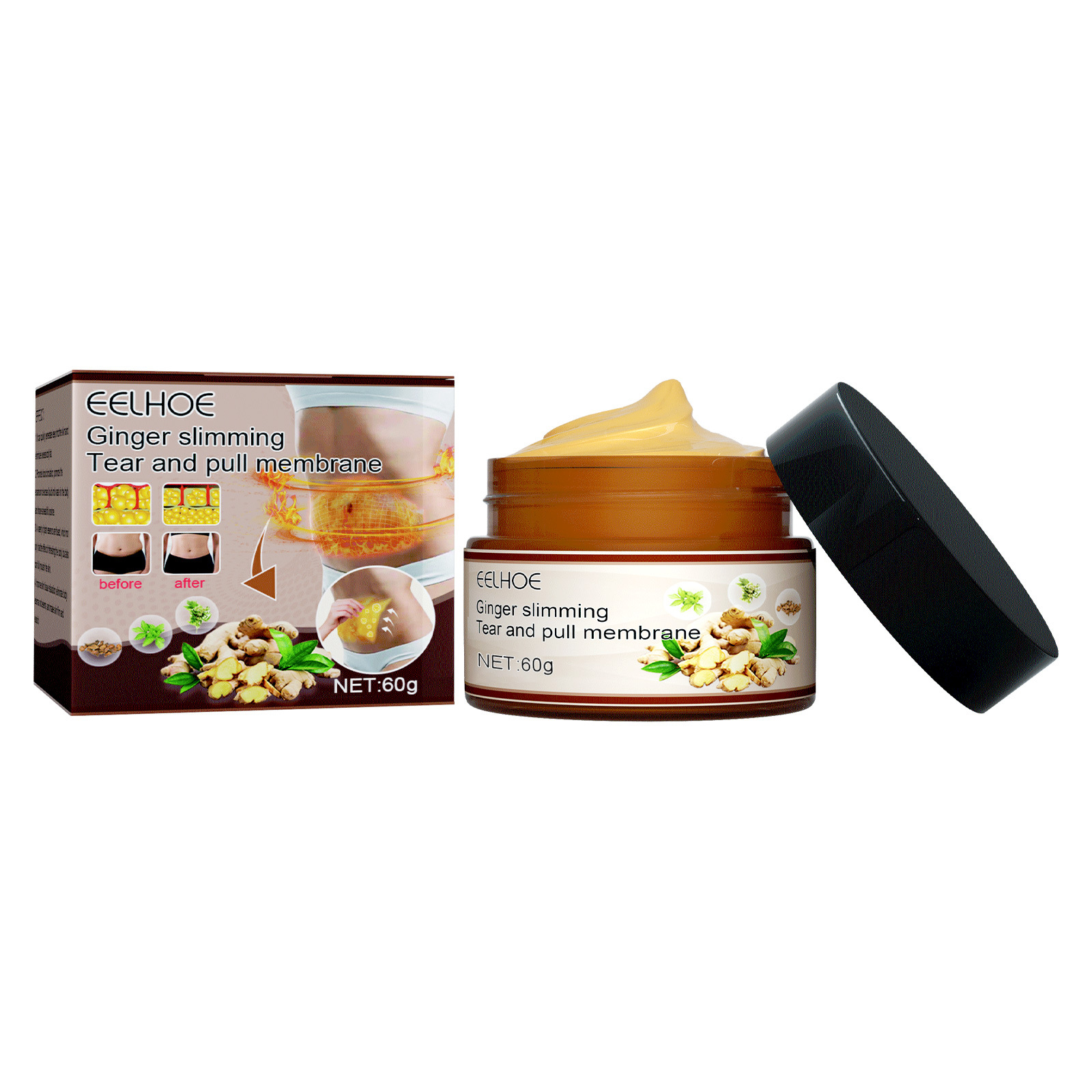 DRUG LABEL: Ginger slimming Tear and pull membrane
NDC: 83675-021 | Form: CREAM
Manufacturer: Guangzhou Hanhai Trading Co., Ltd
Category: otc | Type: HUMAN OTC DRUG LABEL
Date: 20231007

ACTIVE INGREDIENTS: GINGER 18 g/100 g
INACTIVE INGREDIENTS: LEONURUS CARDIACA FLOWERING TOP; LICORICE; MORUS ALBA LEAF

Active Ingredient

Ginger 18.0%

Purpose

Slimming

Use

Eliminate edema
Tighten the arm
Slender and smooth

Warnings

For external use only. Do not take it internally.

Keep Out Of Reach Of Children
Sensitive Skin

Do not use

Product shall not be eat

When Using

Apply the product to the part you need.After about 40 minutes, it can be torn off when it forms a film.

Stop Use

In case of adverse reactions, please stop using this product.If the symptoms.

Ask Doctor

ask doctor in case of Sensitive Skin

Keep Oot Of Reach Of Children

Keep Out Of Reach Of Children

Directions

Apply the product to the part you need.After about 40 minutes, it can be torn off when it forms a film.

Other information

Store the product in a cool, dry and well-ventilated place

Avoid direct sunlight

Inactive ingredients

Motherwort
Licorice root powder
Mulberry leaf extract